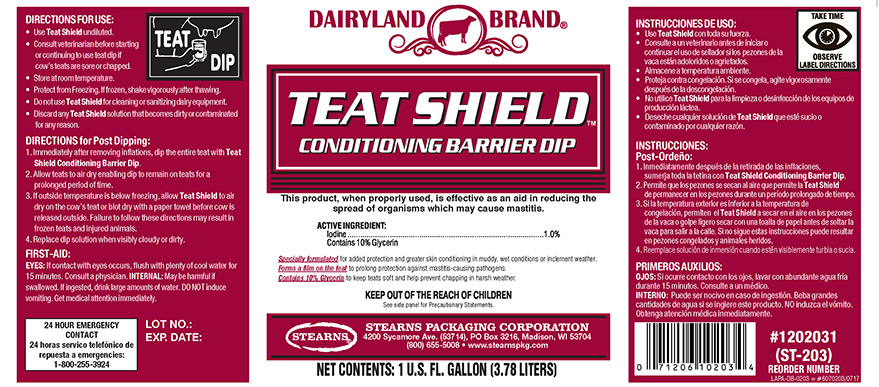 DRUG LABEL: Dairyland Brand Teat Shield Conditioning Barrier Dip
NDC: 60282-1210 | Form: LIQUID
Manufacturer: Stearns Packaging Corporation
Category: animal | Type: OTC ANIMAL DRUG LABEL
Date: 20251201

ACTIVE INGREDIENTS: IODINE 10 g/1 L
INACTIVE INGREDIENTS: GLYCERIN; WATER

Teat Shield Conditioning Barrier Dip

DOSAGE AND ADMINISTRATION

DIRECTIONS FOR USE:
• Use Teat Shield undiluted.
• Consult veterinarian before starting or continuing to use teat dip if cow’s teats are sore or chapped.
• Store at room temperature.
• Protect from Freezing. If frozen, shake vigorously after thawing.
• Do not use Teat Shield for cleaning or sanitizing dairy equipment.
• Discard any Teat Shield solution that becomes dirty or contaminated for any reason.

DIRECTIONS for Post Dipping:
1. Immediately after removing inflations, dip the entire teat with Teat Shield Conditioning Barrier Dip.
2. Allow teats to air dry enabling dip to remain on teats for a prolonged period of time.
3. If outside temperature is below freezing, allow Teat Shield to air dry on the cow’s teat or blot dry with a paper towel before cow is
released outside. Failure to follow these directions may result in frozen teats and injured animals.
4. Replace dip solution when visibly cloudy or dirty.

USER SAFETY WARNINGS

FIRST AID:
EYES: If contact with eyes occurs, flush with plenty of cool water for 15 minutes. Consult a physician.
INTERNAL: May be harmful if swallowed. If ingested, drink large amounts of water. DO NOT induce vomiting. Drink large
quantities of water. See physician immediately. Get medical attention immediately.

24 HOUR EMERGENCY CONTACT

1-800-255-3924

PACKAGE LABEL

DAIRYLAND BRAND

TEAT SHIELD
CONDITIONING BARRIER DIP

This product, when properly used, is effective as an aid in reducing the spread of organisms which may cause mastitis.

ACTIVE INGREDIENT:
Iodine............................................................1.0%
Contains 10% Glycerin

Specially formulated for added protection and greater skin conditioning in muddy, wet conditions or inclement weather.
Forms a film on the teat to prolong protection against mastitis-causing pathogens.
Contains 10% Glycerin to keep teats soft and help prevent chapping in harsh weather.

KEEP OUT OF THE REACH OF CHILDREN
See side panel for Precautionary Statements.

STEARNS PACKAGING CORPORATION
4200 Sycamore Ave. (53714), PO Box 3216,Madison, Wisconsin 53704

(800) 655-5008 • www.stearnspkg.com
NET CONTENTS: 1 U.S. FL. GALLON (3.78 LITERS)